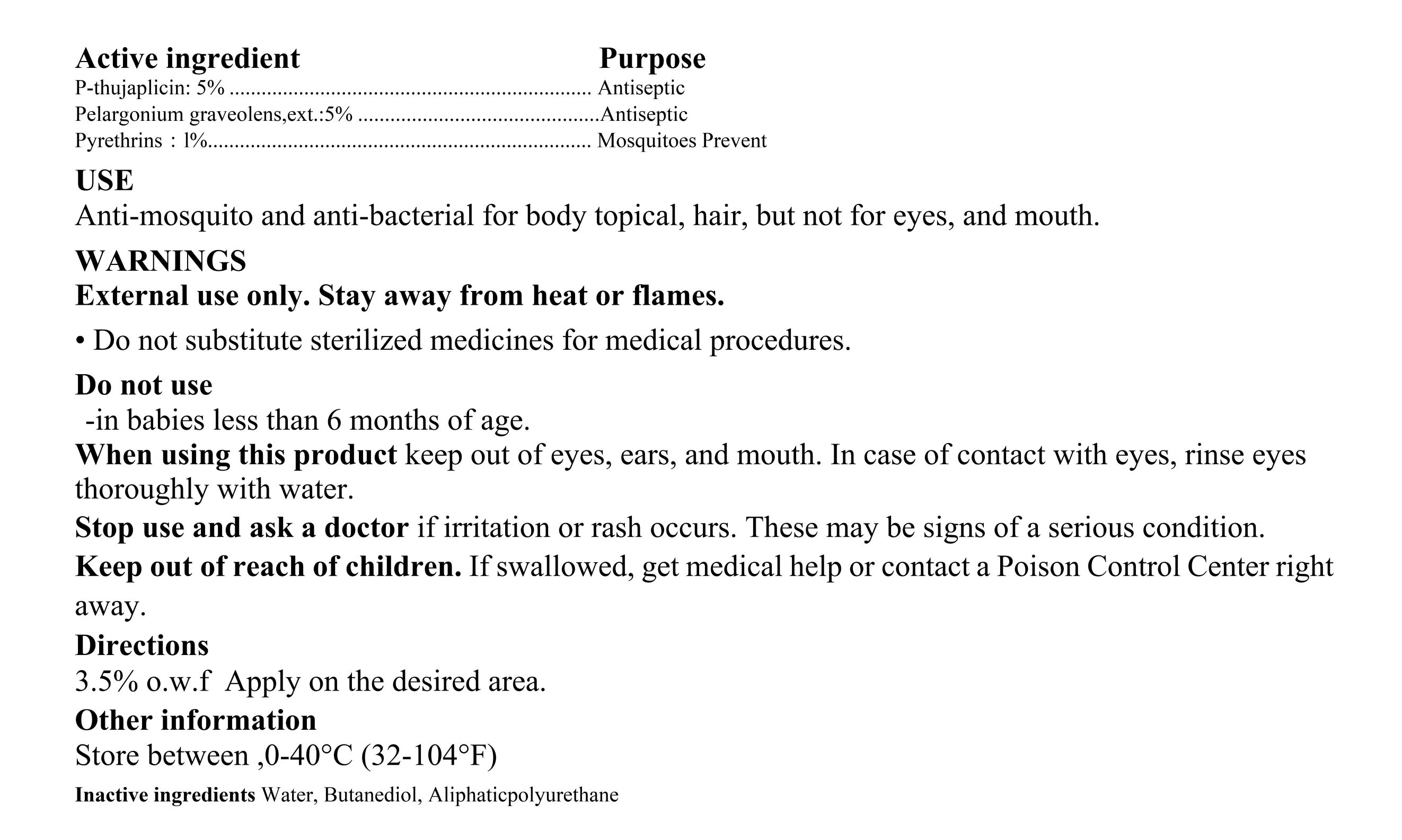 DRUG LABEL: Mosquitoes Prevent
NDC: 83141-1001 | Form: LIQUID
Manufacturer: Jiangsu New Reba Technology Inc.
Category: otc | Type: HUMAN OTC DRUG LABEL
Date: 20221220

ACTIVE INGREDIENTS: PYRETHRUM EXTRACT 0.01 kg/1 kg
INACTIVE INGREDIENTS: POLYURETHANE-62; PELARGONIUM GRAVEOLENS FLOWERING TOP; WATER; .BETA.-THUJAPLICIN; BUTYLENE GLYCOL

NewReba, Mosquitoes Prevent, Liquid, 1% Pyrethrins, 60kg

Active Ingredient(s)

β-thujaplicin, 5% w/w, Antiseptic

Pelargonium graveolens,ext., 5% w/w, Antiseptic

Pyrethrins, 1% w/w, Mosquitoes Prevent

Purpose

β-thujaplicin, Antiseptic

Pelargonium graveolens,ext., Antiseptic

Pyrethrins, Mosquitoes Prevent

Use

Anti-mosquito and anti-bacterial for body topical, hair, but not for eyes, and mouth.

Warnings

External use only. Stay away from heat or flames.

- Do not substitute sterilized medicines for medical procedures.

Do not use

- in babies less than 6 months of age.

When using this product

keep out of eyes, ears, and mouth. In case of contact with eyes, rinse eyes thoroughly with water.

Stop use and ask a doctor

if irritation or rash occurs. These may be signs of a serious condition.

Keep out of reach of children

If swallowed, get medical help or contact a Poison Control Center right away.

Directions

3.5% o.w.f Apply on the desired area.

Other information

Store between 0-40℃ (32-104℉)

Inactive ingredients

Water, Butanediol, Aliphaticpolyurethane